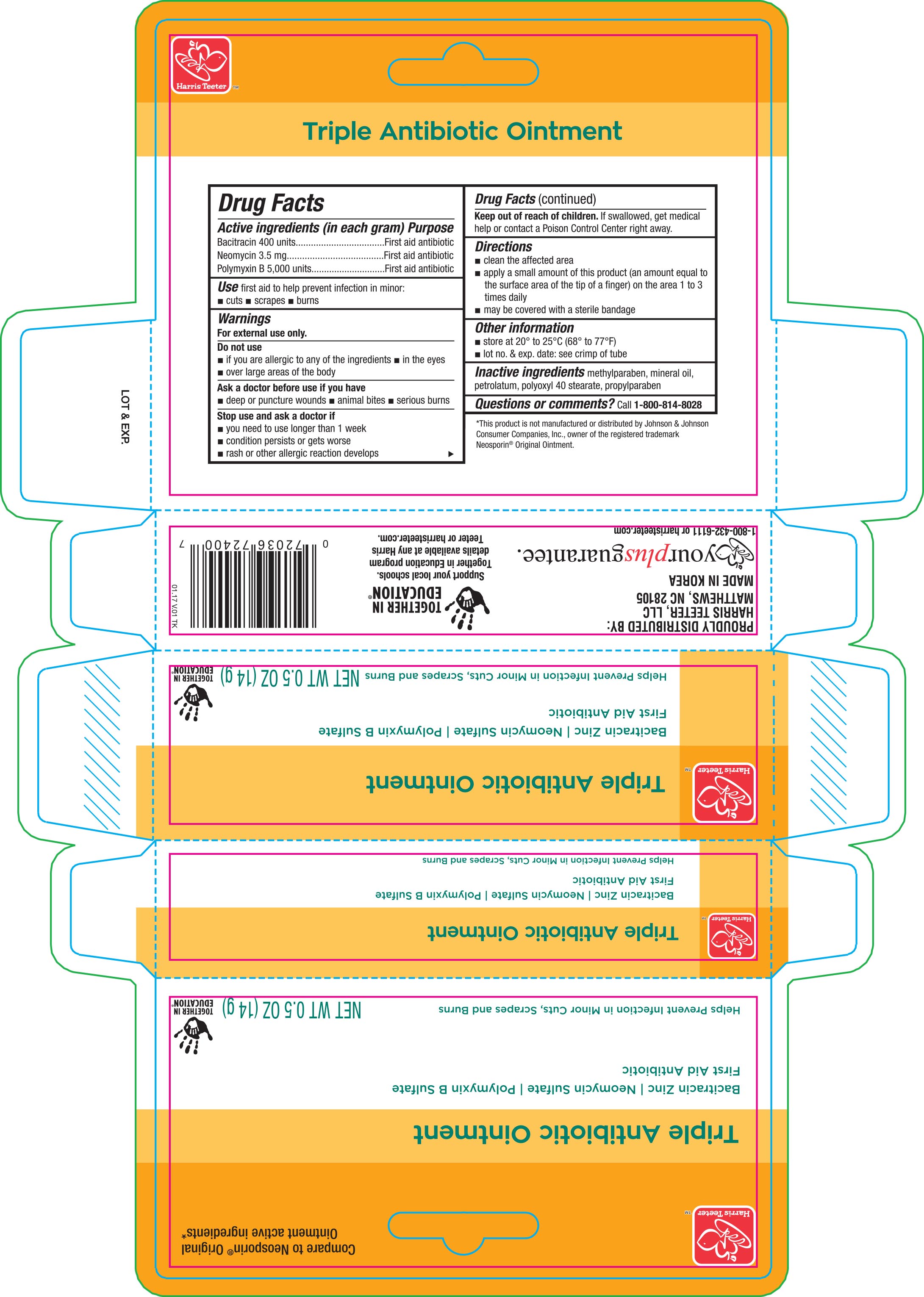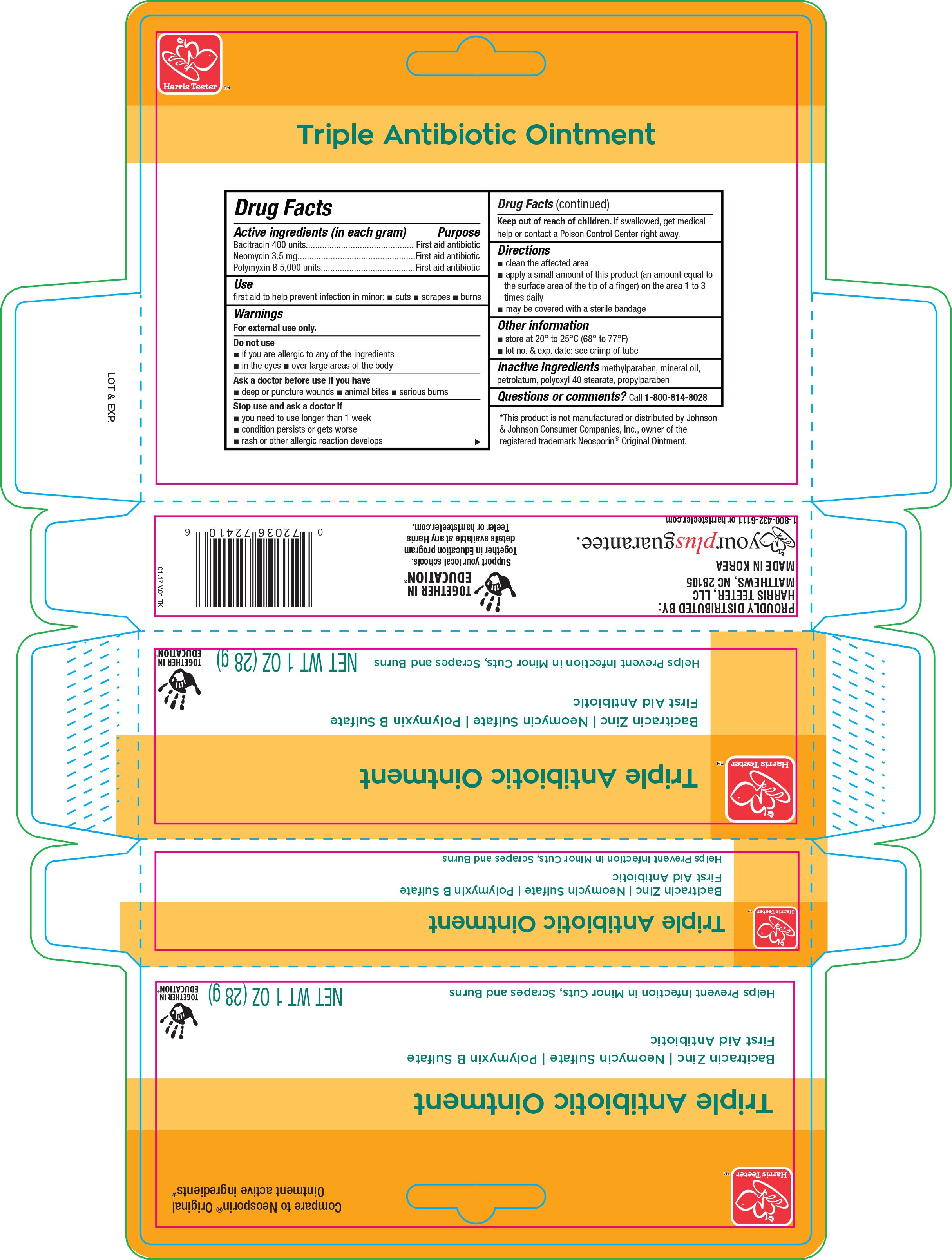 DRUG LABEL: Harris Teeter Triple Antibioitic
NDC: 72036-400 | Form: OINTMENT
Manufacturer: Harris Teeter
Category: otc | Type: HUMAN OTC DRUG LABEL
Date: 20170418

ACTIVE INGREDIENTS: BACITRACIN ZINC 400 [iU]/1 g; NEOMYCIN SULFATE 3.5 mg/1 g; POLYMYXIN B SULFATE 5000 [iU]/1 g
INACTIVE INGREDIENTS: METHYLPARABEN; MINERAL OIL; PETROLATUM; POLYOXYL 40 STEARATE; PROPYLPARABEN

Active ingredients (in each gram) Purpose

Bacitracin 400 units......................................................First aid antibiotic

Neomycin 3.5 mg.........................................................First aid antibiotic

Polymyxin B 5,000 units................................................First aid antibiotic

Use

First aid to help prevent infection in minor:

- cuts
- scrapes
- burns

Warnings

For external use only.

Do not use

- if you are allergic to any of the ingredients
- in the eyes
- over large areas of the body

Ask a doctor before use if you have

- deep or puncture wounds
- animal bites
- serious burns

Stop use and ask a doctor if

- you need to use longer than 1 week
- condition persists or gets worse
- rash or other allergic reaction develops

Keep out of reach of children. If swallowed, get medical help or contact a Poison Control Center right away.

Directions

- clean the affected area
- apply a small amount of this product (an amount equal to the surface area of the tip of a finger) on the area 1 to 3 times daily
- may be covered with a sterile bandage

Other information

- store at 20° to 25°C (68° to 77°F)
- lot no. & exp. date: see crimp of tube

Inactive ingredients

methylparaben, mineral oil, petrolatum, polyoxyl 40 stearate, propylparaben

DOSAGE AND ADMINISTRATION

Distributed by:

Harris Teeter, LLC

Matthews, NC 28105

Made in Korea